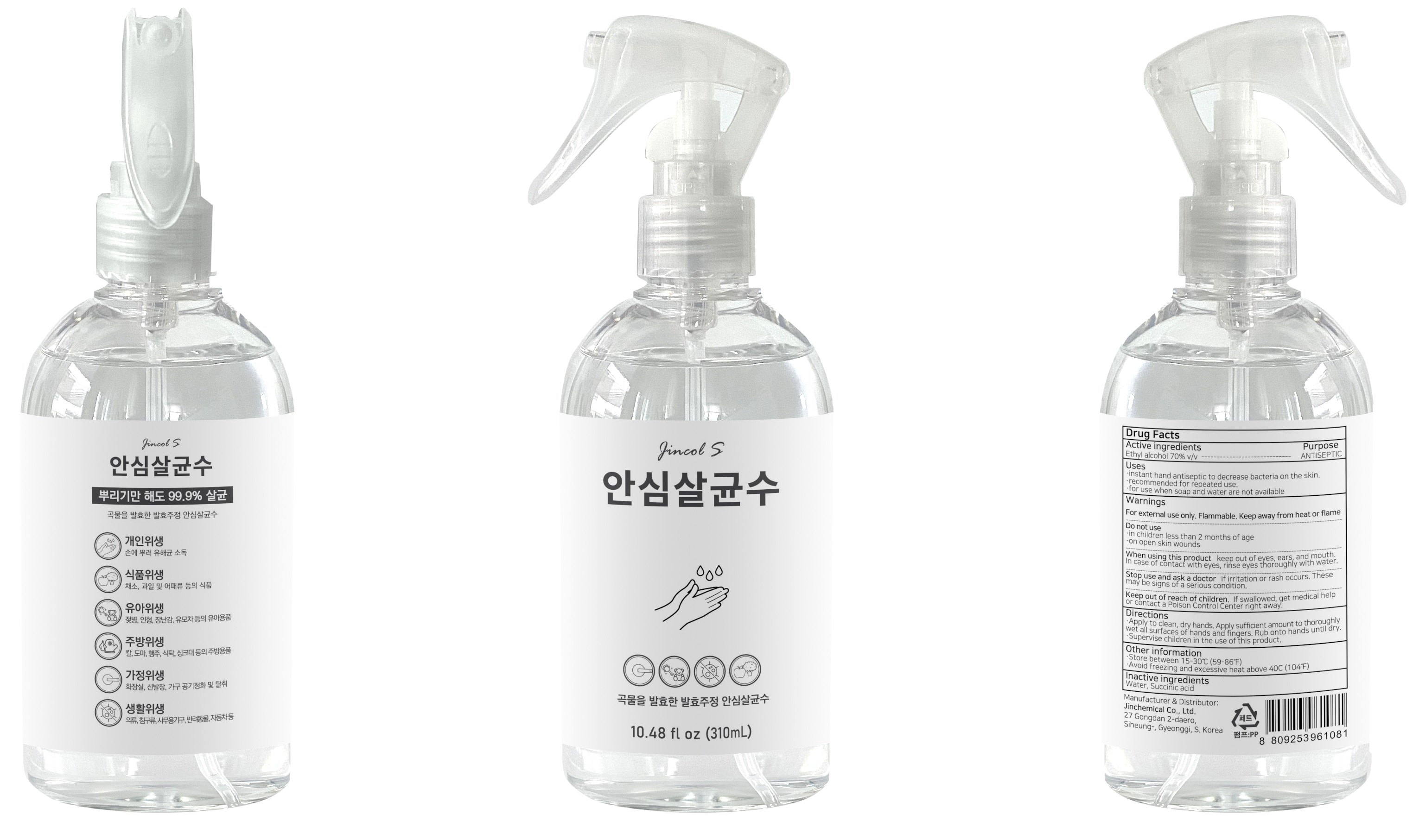 DRUG LABEL: Jincol S
NDC: 79510-010 | Form: SPRAY
Manufacturer: Jinchemical Co., Ltd.
Category: otc | Type: HUMAN OTC DRUG LABEL
Date: 20200714

ACTIVE INGREDIENTS: ALCOHOL 70 mL/100 mL
INACTIVE INGREDIENTS: WATER; SUCCINIC ACID

ACTIVE INGREDIENT

Ethyl alcohol 70% v/v

INACTIVE INGREDIENTS

Water, Succinic acid

PURPOSE

ANTISEPTIC

WARNINGS

For external use only. Flammable. Keep away from heat or flame
--------------------------------------------------------------------------------------------------------
Do not use
• in children less than 2 months of age
• on open skin wounds
--------------------------------------------------------------------------------------------------------
When using this product keep out of eyes, ears, and mouth. In case of contact with eyes, rinse eyes thoroughly with water.
--------------------------------------------------------------------------------------------------------
Stop use and ask a doctor if irritation or rash occurs. These may be signs of a serious condition.

KEEP OUT OF REACH OF CHILDREN

If swallowed, get medical help or contact a Poison Control Center right away.

Uses

•instant hand antiseptic to decrease bacteria on the skin.
•recommended for repeated use.
•for use when soap and water are not available

Directions

• Apply to clean, dry hands. Apply sufficient amount to thoroughly wet all surfaces of hands and fingers. Rub onto hands until dry.
• Supervise children in the use of this product.

Other Information

• Store between 15-30℃ (59-86℉)
• Avoid freezing and excessive heat above 40C (104℉)